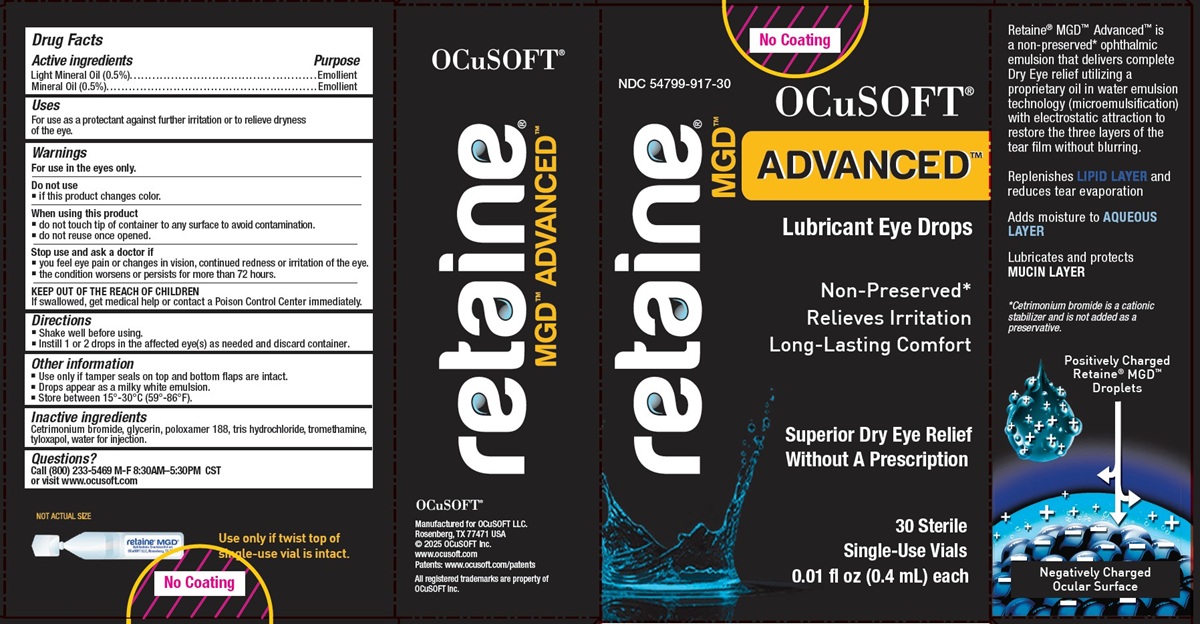 DRUG LABEL: retaine MGD
NDC: 54799-917 | Form: EMULSION
Manufacturer: OCuSOFT LLC
Category: otc | Type: HUMAN OTC DRUG LABEL
Date: 20260115

ACTIVE INGREDIENTS: LIGHT MINERAL OIL 2 mg/0.4 mL; MINERAL OIL 2 mg/0.4 mL
INACTIVE INGREDIENTS: Cetrimonium Bromide; GLYCERIN; POLOXAMER 188; TROMETHAMINE HYDROCHLORIDE; TROMETHAMINE; TYLOXAPOL; WATER

Drug Facts

Active ingredients

Light Mineral Oil (0.5%)
Mineral Oil (0.5%)

Purpose

Emollient

Uses

For use as a protectant against further irritation or to relieve dryness of the eye.

Warnings

For use in the eyes only.

Do not use

- if this product changes color.

When using this product

- do not touch tip of container to any surface to avoid contamination.
- do not reuse once opened.

Stop use and ask a doctor if

- you feel eye pain or changes in vision, continued redness or irritation of the eye.
- the condition worsens or persists for more than 72 hours.

KEEP OUT OF THE REACH OF CHILDREN

If swallowed, get medical help or contact a Poison Control Center immediately.

Directions

- Shake well before using.
- Instill 1 or 2 drops in the affected eye(s) as needed and discard container.

Other information

- Use only if tamper seals on top and bottom flaps are intact.
- Drops appear as a milky white emulsion.
- Store between 15 o-30 oC (59 o-86 oF).

Inactive ingredients

Cetrimonium Bromide, glycerin, poloxamer 188, tris hydrochloride, tromethamine, tyloxapol, water for injection.

Questions?

Call (800) 233-5469 M-F 8:30AM-5:30PM CST
or visit www.ocusoft.com

PRINCIPAL DISPLAY PANEL - 30 sterile Single-Dose Containers

NDC 54799-917-30
OCuSOFT®
MGD™
ADVANCED™
Lubricant Eye Drops
Non-Preserved*
Relieves Irritation
Long-Lasting Comfort
Superior Dry Eye Relief
Without A Prescription
30 Sterile
Single-Dose Vials
0.01 fl oz (0.4 mL) each
Retaine® MGD™ Advanced™ is
a non-preserved* ophthalmic
emulsion that delivers complete
Dry Eye relief utilizing a
proprietary oil in water emulsion
technology (microemulsification)
with electrostatic attraction to
restore the three layers of the
tear film without blurring.
Replenishes LIPID LAYER and
reduces tear evaporation
Adds moisture to AQUEOUS
LAYER
Lubricates and protects
MUCIN LAYER
*Cetrimonium bromide is a cationic
stabilizer and is not added as a
preservative.
Positively Charged
Retaine® MGD™
Droplets
Negatively Charged
Ocular Surface
Use only if twist top of
single-dose vial is intact.
OCuSOFT®
Manufactured for OCuSOFT LLC.
Rosenberg, TX 77471 USA
© 2025 OCuSOFT Inc.
www.ocusoft.com
Patents: www.ocusoft.com/patents
All registered trademarks are property of
OCuSOFT Inc.